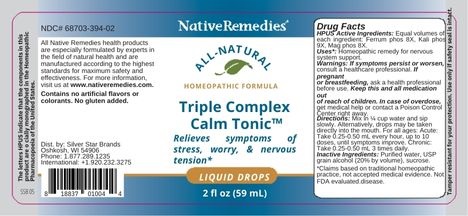 DRUG LABEL: NativeRemedies Triple Complex Calm Tonic
NDC: 68703-394 | Form: LIQUID
Manufacturer: Silver Star Brands
Category: homeopathic | Type: HUMAN OTC DRUG LABEL
Date: 20250101

ACTIVE INGREDIENTS: MAGNESIUM PHOSPHATE, DIBASIC TRIHYDRATE 8 [hp_X]/59 mL; POTASSIUM PHOSPHATE, DIBASIC 9 [hp_X]/59 mL; FERROSOFERRIC PHOSPHATE 8 [hp_X]/59 mL
INACTIVE INGREDIENTS: WATER; ALCOHOL

NativeRemedies® Triple Complex Calm Tonic™

HPUS Active Ingredients: Ferrum phos 8X, Kali phos 9X, Mag phos 8X.

The letters HPUS indicate that the components in this product are officially monographed in the Homeopathic Pharmacopoeia of the United States.

Uses*

Uses*: Homeopathic remedy for nervous system support.

*Claims based on traditional homeopathic practice, not accepted medical evidence. Not FDA evaluated disease.

Warnings

Warnings: If symptoms persist or worsen, consult a healthcare professional. If pregnant or breastfeeding, ask a health professional before use. Keep this and all medication out of reach of children. In case of overdose, get medical help or contact a Poison Control Center right away.

Directions

Directions: Mix in 1/4 cup water and sip slowly. Alternatively, drops may be taken directly into the mouth. For all ages: Acute: Take 0.25-0.50 mL every hour, up to 10 doses, until symptoms improve. Chronic: Take 0.25-0.50 mL 3 times daily.

OTHER SAFETY INFORMATION

Contains no artificial flavors or colorants. No gluten added.

Tamper resistent for your protection. Use only if safety seal is intact.

Inactive Ingredients

Inactive Ingredients: Purified water, USP grain alcohol (20% by volume), sucrose.

KEEP OUT OF REACH OF CHILDREN

Keep this and all medication out of reach of children.

PREGNANCY OR BREAST FEEDING

If pregnant or breastfeeding, ask a health professional before use.

PURPOSE

Relieves symptoms of stress, worry, & nervous tension.